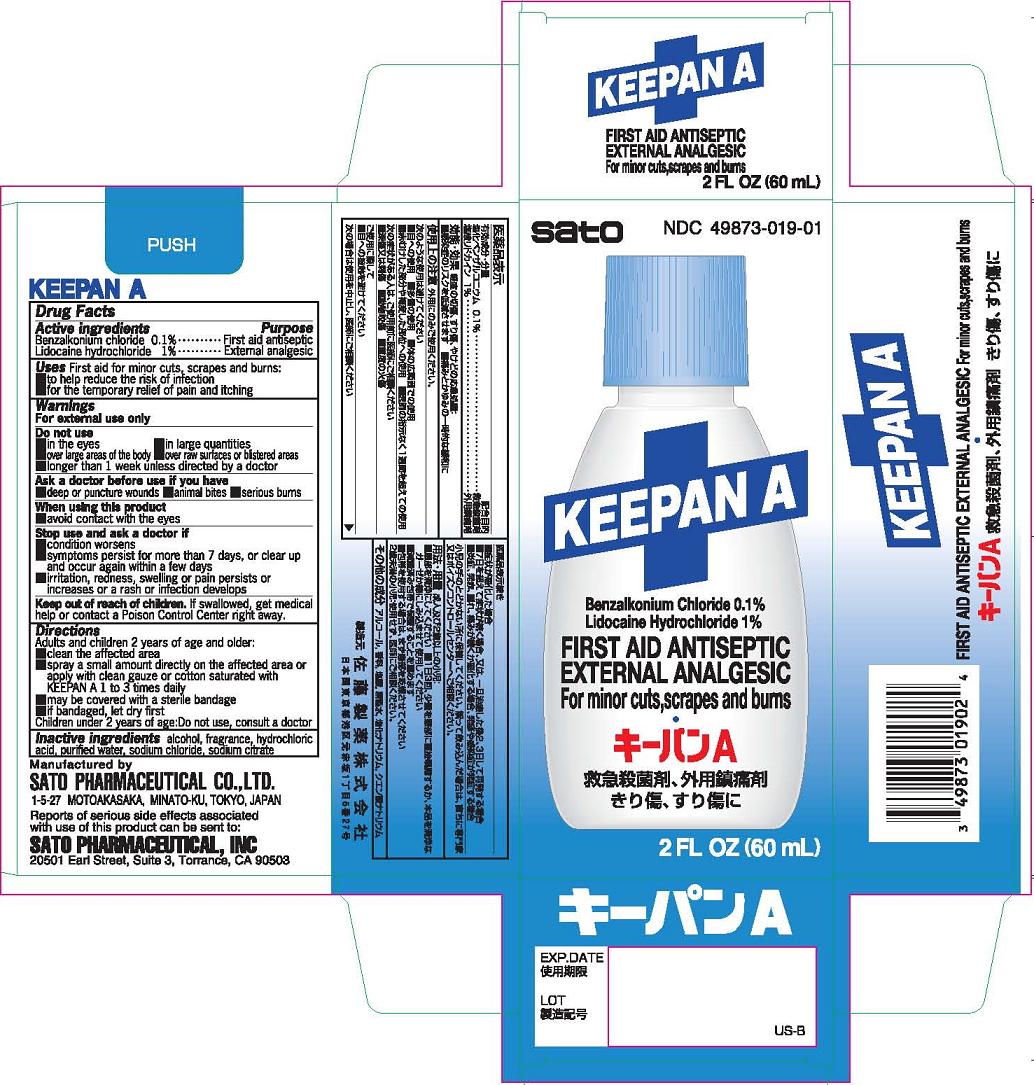 DRUG LABEL: KEEPAN A
NDC: 49873-019 | Form: SPRAY
Manufacturer: Sato Pharmaceutical Co., Ltd.
Category: otc | Type: HUMAN OTC DRUG LABEL
Date: 20241230

ACTIVE INGREDIENTS: BENZALKONIUM CHLORIDE 0.1 g/100 mL; LIDOCAINE HYDROCHLORIDE 1 g/100 mL
INACTIVE INGREDIENTS: ALCOHOL; HYDROCHLORIC ACID; WATER; SODIUM CHLORIDE; TRISODIUM CITRATE DIHYDRATE

Keepan A

Active ingredients
Benzalkonium chloride 0.1%
Lidocaine hydrochloride 1%

Purpose
Benzalkonium chloride First aid antiseptic
Lidocaine hydrochloride External analgesic

INDICATIONS AND USAGE

Uses First aid for minor cuts, scrapes and burns:
■ to help reduce the risk of infection
■ for the temporary relief of pain and itching

Warnings
For external use only

Do not use
■ in the eyes ■ in large quantities
■ over large areas of the body ■ over raw surfaces or blistered areas
■ longer than 1 week unless directed by a doctor

Ask a doctor before use if you have
■ deep or puncture wounds ■ animal bites ■ serious burns

When using this product
■ avoid contact with the eyes

Stop use and ask a doctor if
■ condition worsens
■ symptoms persist for more than 7 days, or clear up and occur again within a few days
■ irritation, redness, swelling or pain persists or increases or a rash or infection develops

Keep out of reach of children. If swallowed, get medical help or contact a Poison Control Center right away.

Directions
Adults and children 2 years of age and older:
■ clean the affected area
■ spray a small amount directly on the affected area or apply with clean gauze or cotton saturated with KEEPAN A 1 to 3 times daily
■ may be covered with a sterile bandage
■ if bandaged, let dry first
Children under 2 years of age: Do not use, consult a doctor.

INACTIVE INGREDIENT

Inactive ingredients alcohol, fragrance, hydrochloric acid, purified water, sodium chloride, sodium citrate